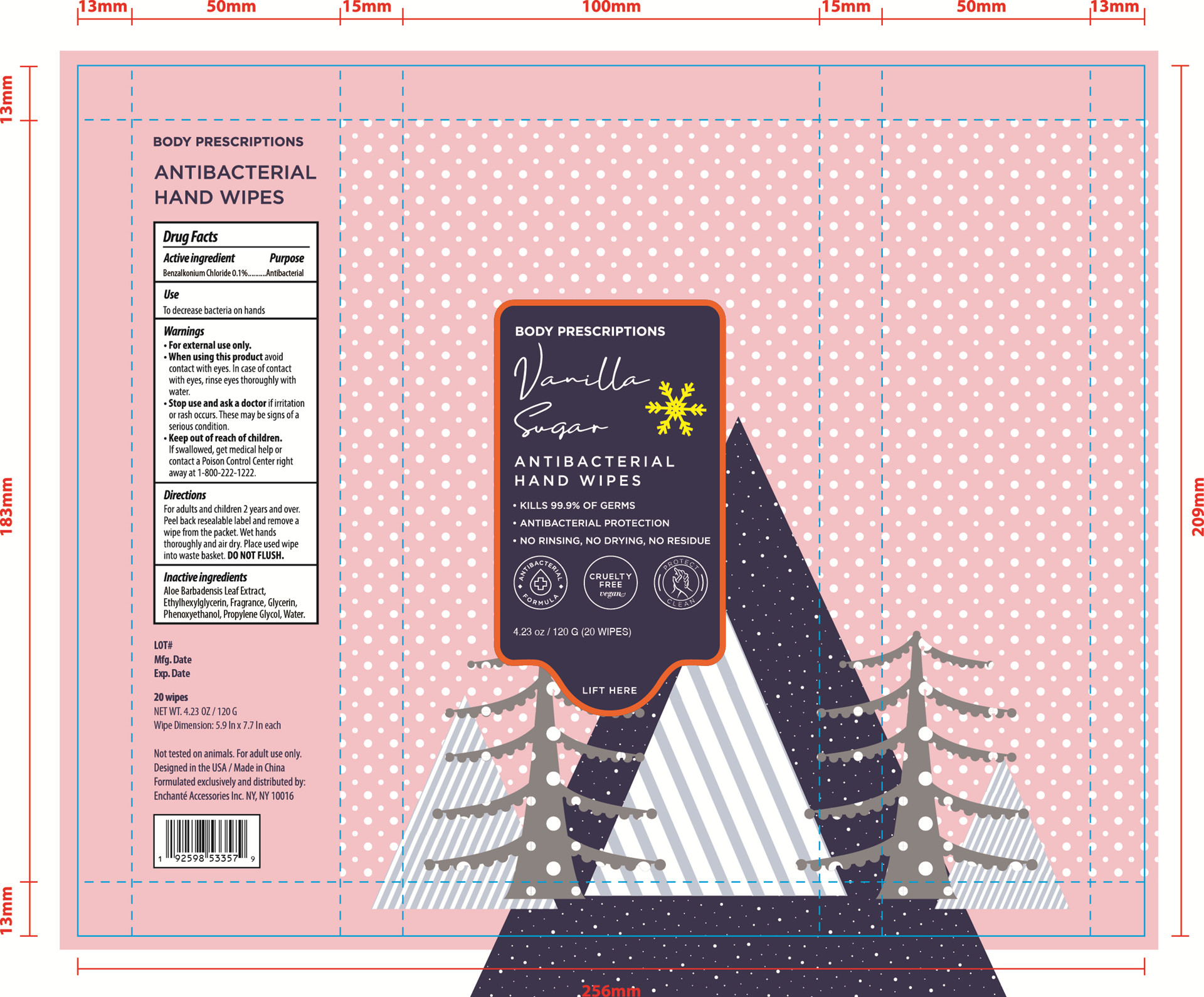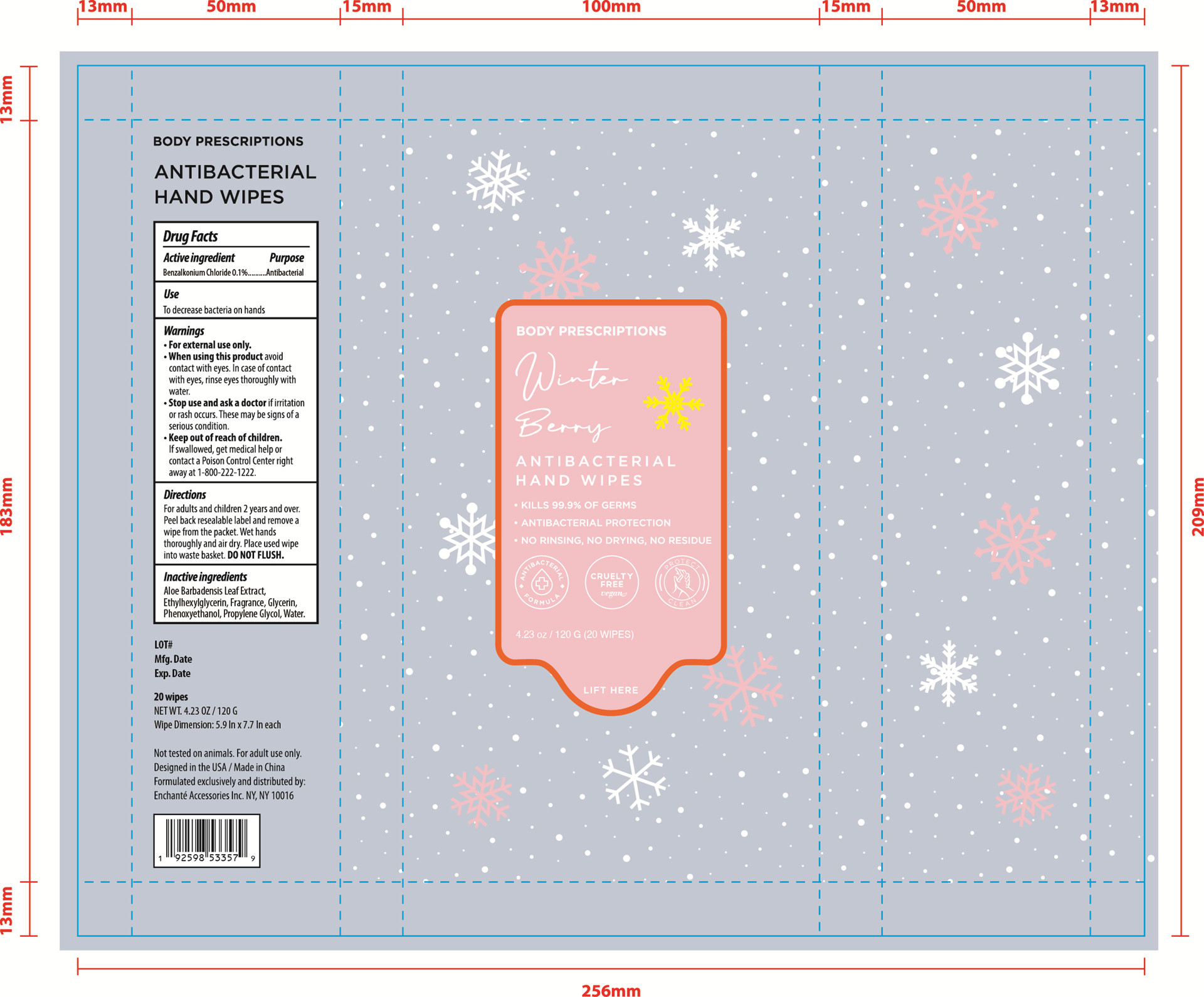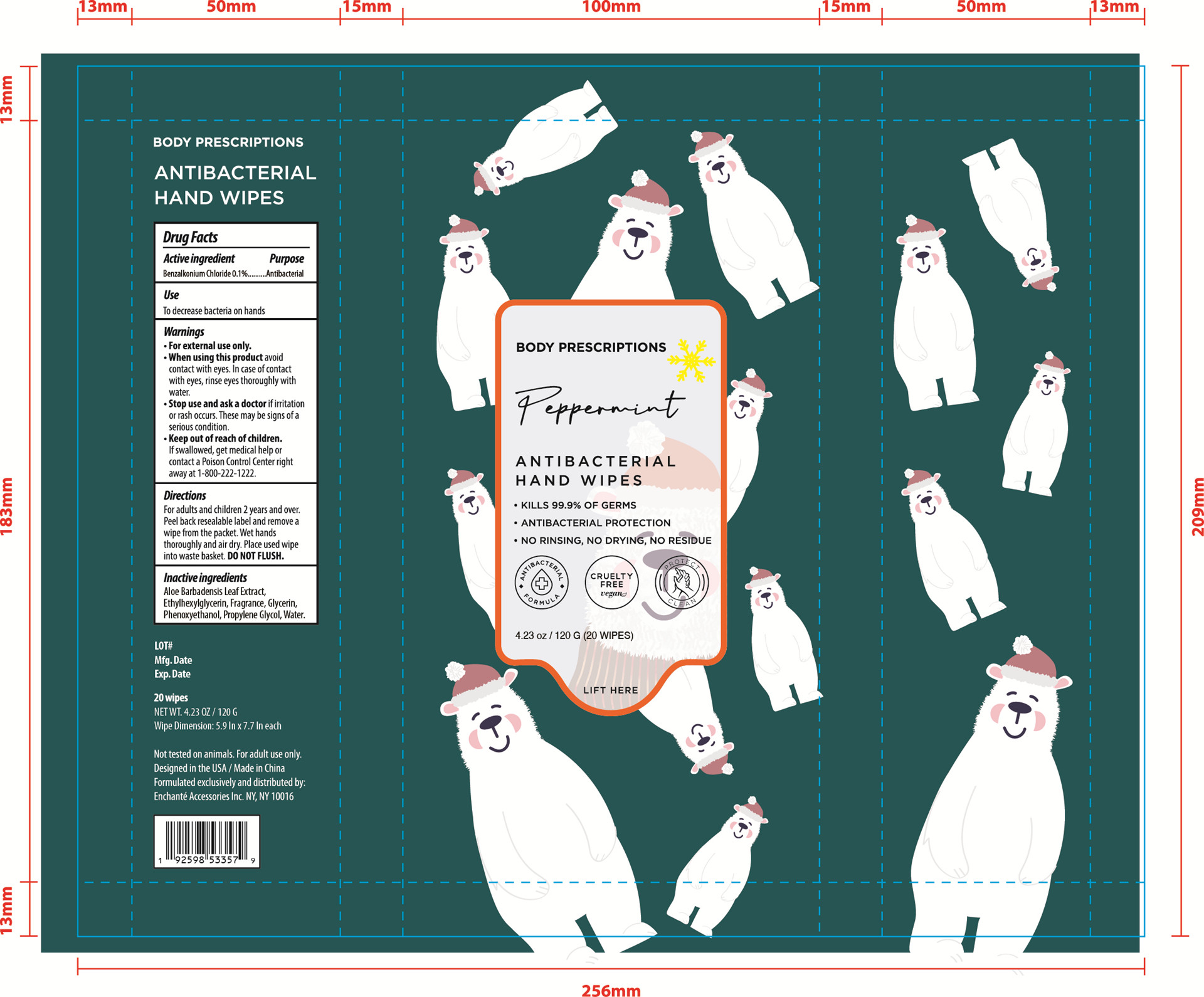 DRUG LABEL: BODY PRESCRIPTIONS ANTIBACTERIAL HAND WIPES Vanilla Sugar Winter Berry Peppermint
NDC: 50563-362 | Form: KIT | Route: TOPICAL
Manufacturer: ENCHANTE ACCESSORIES INC.
Category: otc | Type: HUMAN OTC DRUG LABEL
Date: 20201020

ACTIVE INGREDIENTS: BENZALKONIUM CHLORIDE 4.5 mg/1 1; BENZALKONIUM CHLORIDE 4.5 mg/1 1; BENZALKONIUM CHLORIDE 4.5 mg/1 1
INACTIVE INGREDIENTS: WATER; GLYCERIN; ETHYLHEXYLGLYCERIN; PHENOXYETHANOL; PROPYLENE GLYCOL; ALOE VERA LEAF; WATER; GLYCERIN; ETHYLHEXYLGLYCERIN; PHENOXYETHANOL; PROPYLENE GLYCOL; ALOE VERA LEAF; WATER; GLYCERIN; ETHYLHEXYLGLYCERIN; PHENOXYETHANOL; PROPYLENE GLYCOL; ALOE VERA LEAF

50563-359/360/361/362 G0XABW03

BODY PRESCRIPTIONS ANTIBACTERIAL HAND WIPES Vanilla Sugar

Active Ingredient

Benzalkonium Chloride 0.1%

Purpose

Antibacterial

Use

■ To decrease bacteria on hands

WARNINGS

For external use only

When using this product avoid contact with eyes. In case of contact with eyes, rinse thoroughly with water

Stop use and ask a doctor if irritation or rash occurs. This may be signs of a serious condition

Keep out of reach of children. If swallowed, get medical help or contact a Poison Control Center right away at 1-800-222-1222

Directions

For adults and children two years and over

Peel over reusable label and remove a wipe from the packet.

Wet hands thoroughly and air dry.

Place used wipes into waste basket. Do not flush.

Inactive ingredients

Aloe Barbadensis Leaf Extract, Ethylhexylglycerin, Fragrance, Glycerin, Phenoxyethanol, Propylene Glycol, Water

BODY PRESCRIPTIONS ANTIBACTERIAL HAND WIPES Winter Berry

Active Ingredient

Benzalkonium Chloride 0.1%

Purpose:

Antibacterial

Uses:

■ To decrease bacteria on hands

Warnings

For external use only

When using this product avoid contact with eyes. In case of contact with eyes, rinse thoroughly with water

Stop use and ask a doctor if irritation or rash occurs. This may be signs of a serious condition

Keep out of reach of children. If swallowed, get medical help or contact a Poison Control Center right away at 1-800-222-1222

Directions

For adults and children two years and over

Peel over reusable label and remove a wipe from the packet.

Wet hands thoroughly and air dry.

Place used wipes into waste basket. Do not flush.

Inactive Ingredients

Aloe Barbadensis Leaf Extract, Ethylhexylglycerin, Fragrance, Glycerin, Phenoxyethanol, Propylene Glycol, Water

BODY PRESCRIPTIONS ANTIBACTERIAL HAND WIPES Peppermint

Active Ingredient

Benzalkonium Chloride 0.1%

Purpose

Antibacterial

Uses

■ To decrease bacteria on hands

Warnings

For external use only

When using this product avoid contact with eyes. In case of contact with eyes, rinse thoroughly with water

Stop use and ask a doctor if irritation or rash occurs. This may be signs of a serious condition

Keep out of reach of children. If swallowed, get medical help or contact a Poison Control Center right away at 1-800-222-1222

Directions

For adults and children two years and over

Peel over reusable label and remove a wipe from the packet.

Wet hands thoroughly and air dry.

Place used wipes into waste basket. Do not flush.

Inactive Ingredients

Aloe Barbadensis Leaf Extract, Ethylhexylglycerin, Fragrance, Glycerin, Phenoxyethanol, Propylene Glycol, Water